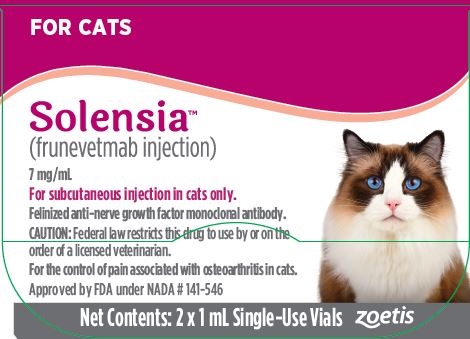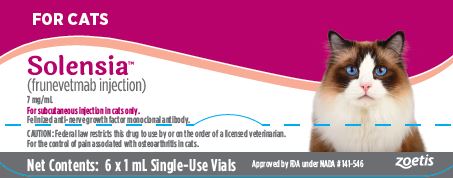 DRUG LABEL: Solensia
NDC: 54771-3520 | Form: SOLUTION
Manufacturer: Zoetis Inc.
Category: animal | Type: PRESCRIPTION ANIMAL DRUG LABEL
Date: 20221123

ACTIVE INGREDIENTS: FRUNEVETMAB 7 mg/1 mL

SolensiaTM

SolensiaTM
(frunevetmab injection)
7 mg/mL
Feline anti-nerve growth factor monoclonal antibody for subcutaneous injection in cats only.
Single-Use Vial

CAUTION

Federal law restricts this drug to use by or on the order of a licensed veterinarian.

DESCRIPTION

SOLENSIA (frunevetmab injection) is a sterile injectable solution containing 7 mg/mL of frunevetmab in histidine buffer (10 mM L-histidine monohydrochloride, 5% D-sorbitol, 0.01% polysorbate 20, adjusted to pH 6.0 by HCl/NaOH, quantity sufficient to 1 mL by Water for Injection.). Frunevetmab is a felinized immunoglobulin G monoclonal antibody (mAb), a murine antibody in which all regions of the mouse antibody are replaced with feline counterparts except for the complementarity-determining regions. Frunevetmab binds to nerve growth factor (NGF) to block NGF’s effects. Such mAbs are commonly referred to as anti-NGF mAbs.

INDICATION

SOLENSIA is indicated for the control of pain associated with osteoarthritis in cats.

DOSAGE AND ADMINISTRATION

Cats should be dosed by weight range according to the Dosing Chart (Table 1) below. Cats are given the full content of 1 or 2 vials based on body weight to target a minimum dosage of 0.45 mg/lb. (1 mg/kg) body weight, administered subcutaneously once a month. Aseptically withdraw the total dose into a single syringe and administer immediately.

The product does not contain a preservative. The full content of each vial is for single use only. Once punctured, contents of the vial should be used immediately and any remaining solution should be discarded.

Table 1. Dosing Chart

Weight of Cat; (lb.) | Weight of Cat; (kg) | Volume | Number of Vials*
5.5‑15.4 | 2.5‑7 kg | 1 mL | 1
15.5‑30.8 | 7.1‑14 kg | 2 mL | 2

*1 mL frunevetmab injection per vial

CONTRAINDICATIONS

SOLENSIA should not be administered to cats with known hypersensitivity to frunevetmab.

SOLENSIA should not be used in breeding cats or in pregnant or lactating queens because it may pass through the placental blood barrier and be excreted in milk. Fetal abnormalities, increased rates of stillbirths and increased postpartum fetal mortality were noted in rodents and primates receiving anti‑NGF mAbs.

WARNINGS

User Safety Warnings

Not for use in humans. Keep out of reach of children.

Hypersensitivity reactions, including anaphylaxis, could potentially occur in the case of accidental self-injection.

In case of accidental self-injection, seek medical advice immediately and show the package leaflet or the label to the physician.

Pregnant women, women trying to conceive, and breastfeeding women should take extreme care to avoid accidental self-injection.

The importance of NGF in ensuring normal fetal nervous system development is well-established and laboratory studies conducted on nonhuman primates with human anti‑NGF antibodies have shown evidence of reproductive and developmental toxicity

PRECAUTIONS

Administration of mAbs may be associated with hypersensitivity reactions and delayed hypersensitivity reactions. If anaphylaxis or other hypersensitivity reaction occurs, discontinue use and institute appropriate therapy.

Administration of SOLENSIA may be associated with scabbing on the head and neck, dermatitis, and pruritus; however, preapproval data suggest that these signs do not require cessation of SOLENSIA administration (see ADVERSE REACTIONS and TARGET ANIMAL SAFETY).

Evaluations were not made to determine if interactions occurred between SOLENSIA and veterinary vaccines.

Treatment with SOLENSIA may result in the formation of anti-frunevetmab antibodies and potentially the loss of product effectiveness (see Immunogenicity).

The safe use of SOLENSIA with concurrent non-steroidal anti-inflammatory drugs (NSAIDs) has not been established in cats. In human clinical trials, rapidly progressing osteoarthritis (RPOA) has been reported in a small number of patients receiving humanized anti‑NGF mAb therapy. The incidence of these events increased in human patients receiving NSAID treatment long term in combination with an anti‑NGF mAb.

RPOA has not been characterized or reported in cats.

SOLENSIA has not been evaluated in cats less than 7 months or 5.5 lbs.

Long term effects, which may occur more than 6 months after the use of SOLENSIA, have not been evaluated. Primates receiving high doses of anti-NGF mAbs had reduced cell size in postganglionic neuronal cell bodies. The change in cell body size returned to normal after anti-NGF mAb administration was discontinued. NGF is involved in the normal development of sensory and sympathetic nerve fibers in developing animals. This may be important with use of SOLENSIA in young growing cats.

The safe use of this product with other mAbs has not been evaluated.

ADVERSE REACTIONS

The safety of SOLENSIA was evaluated in a masked, controlled 112‑day field study to evaluate the effectiveness of SOLENSIA for the control of pain associated with osteoarthritis in cats. Enrollment included 275 cats weighing 2.5‑to 11.4 kg and 1.6‑to 22.4 years old; 182 cats were treated with SOLENSIA and 93 cats were administered a vehicle control. Cats were dosed at 28‑day intervals and received up to three injections. The most common adverse reactions reported during the field study are presented below.

Table 2. Adverse Reactions Reported in the Field Study^1

Adverse Reaction | Solensia N=182 (%) | Vehicle Control N=93 (%)
Vomiting | 24 (13.2%) | 10 (10.8%)
Injection site pain^2 | 20 (10.9%) | 13 (14%)
Diarrhea | 12 (6.6%) | 5 (5.4%)
Abnormal behavior and behavioral disorders^3 | 12 (6.6%)^4 | 5 (5.4%)^5
Renal insufficiency^6 | 12 (6.6%) | 4 (4.3%)
Anorexia | 12 (6.6%) | 4 (4.3%)
Lethargy | 11 (6.0%) | 3 (3.2%)
Dermatitis | 11 (6.0%) | 1 (1.1%)
Alopecia | 10 (5.5%) | 2 (2.2%)
Dehydration | 8 (4.4%) | 0 (0.0%)
Lameness^7 | 8 (4.4%) | 2 (2.2%)
Pruritus | 7 (3.8%) | 0 (0.0%)
Weight loss | 6 (3.3%) | 5 (5.4%)
Scabbing on head/neck | 6 (3.3%) | 1 (1.1%)
Gingival disorder | 5 (2.7%) | 0 (0.0%)
Bacterial skin infection | 4 (2.2%) | 1 (1.1%)
Otitis externa | 4 (2.2%) | 0 (0.0%)

^1 If a cat experienced the same event more than once, only the first occurrence is reported
^2 The control product was the vehicle without active ingredient
^3 Behavior abnormal for the individual cat
^4 Individual cats had at least one of the following behavior changes: anxiety (1), hiding (1), hypersomnia (1), inappropriate urination (5), sleeping with owner (1), vocalization (3), increased aggressive behavior (1)
^5 Individual cats had at least one of the following behavior changes: anxiety (2), disorientation (1), inappropriate urination (2), and vocalization (1)
^6 Worsening of existing disease
^7 New lameness or worsening of previous lameness

The safety of SOLENSIA was also evaluated in a masked, controlled 56-day exploratory field study to evaluate the effectiveness of SOLENSIA for the control of pain associated with osteoarthritis in cats. Enrollment included 126 cats; 85 cats were treated with frunevetmab injection manufactured similar to SOLENSIA and 41 cats were administered a vehicle control. Cats were dosed at 28-day intervals and received up to two injections. The most frequently reported adverse reactions were digestive tract disorders, including vomiting and diarrhea, and skin disorders, including dermatitis/eczema and alopecia that were mostly attributed to irritation by an activity monitor collar required for the study.

Immunogenicity
All therapeutic proteins, including monoclonal antibodies, have the potential for immunogenicity, including the production of antibodies that bind to the therapeutic protein and may decrease effectiveness. Such hostderived antibodies are termed anti‑drug antibodies (ADA). SOLENSIA, therefore has the potential to cause the cat to produce ADAs against frunevetmab.
The presence of binding antibodies to frunevetmab in cats was assessed using a screening and confirmatory assay approach. In controlled field effectiveness studies in cats with osteoarthritis (see EFFECTIVENESS), four out of 259 cats that received SOLENSIA once monthly developed anti‑drug antibodies (ADAs). One cat tested positive for ADAs on Days 0, 28, 56, and 84. This cat had non-detectable plasma drug concentration levels of SOLENSIA on Days 28 and 56, and was a treatment failure in the effectiveness analysis, suggesting that the ADAs may have clinical significance. No assessment for neutralizing antibodies was performed.
The observed incidence of antibody positivity in an assay is highly dependent on several factors including assay sensitivity and specificity, assay methodology, sample handling, timing of sample collection, concomitant medications, and underlying disease. For these reasons, comparison of the incidence of antibodies to SOLENSIA with the incidence of antibodies to other products may not be appropriate.

CONTACT INFORMATION

To report suspected adverse drug events, for technical assistance or to obtain a copy of the Safety Data Sheet (SDS), contact Zoetis Inc. at 1-888‑963-8471.
For additional information about reporting adverse drug experiences for animal drugs, contact FDA at 1-888-FDA-VETS or http://www.fda.gov/reportanimalae.

CLINICAL PHARMACOLOGY

Mechanism of Action

Frunevetmab is a felinized monoclonal antibody that binds to nerve growth factor (NGF), reduces NGF binding to the tropomyosin receptor kinase A (TrkA) and p75NTR receptors, and decreases signal transduction in cell types involved in pain. In vitro binding studies suggest that frunevetmab binds with high affinity to NGF, but does not bind to other neurotrophins, including human neurotrophin-3 (NT-3), feline and human neurotrophin-4 (NT-4), and human brain-derived neurotrophic factor (BDNF).
NGF has been found to be elevated in osteoarthritic joints of multiple species. Following a noxious stimulus, inflammatory cytokines and NGF are released by tissues of the joint. NGF binds to TrkA/p75NTR receptors found on peripheral nerves, immune cells, endothelial cells, synoviocytes, and chondrocytes to induce peripheral sensitization, neurogenic inflammation, and increased pain perception.

Frunevetmab binds to NGF and prevents NGF/TrkA/p75NTR cellular signaling. In in vitro studies, frunevetmab potently inhibits NGF-mediated signaling as measured by reducing proliferation of TF-1 cells, a human erythroleukemia cell line, and functionally blocks NGF-induced neurite outgrowth in rat PC-12 neuronal cells.
NGF binds to TrkA receptors located on immune cells to elicit the release of additional proinflammatory mediators, including NGF itself. These inflammatory mediators lead to further peripheral sensitization involved in pain perception. Frunevetmab reduces the expression of these inflammatory mediators in rat PC-12 neuronal cells.

Pharmacokinetics

In a laboratory safety study in healthy cats administered SOLENSIA (frunevetmab injection) subcutaneously once every twenty‑eight days for six consecutive doses (2.8 mg/kg), area under the plasma concentration time curve from time zero to the end of the dose interval (AUC) and maximum plasma concentration (Cmax) increased in a less than dose proportional manner. Dosing every 28 days resulted in minimal accumulation over the course of five consecutive SOLENSIA doses of 2.8 mg/kg.

Table 3. Mean ± Standard Deviation frunevetmab pharmacokinetic parameters following subcutaneous dosing to laboratory and osteoarthritic cats.

Parameter | Laboratory Cats | Osteoarthritic Cats
Dose (mg/kg) | 2.8 | 3.0
Cmax (μg/mL) | 42.8 ± 10.4 | 30.2 ± 5.5
Tmax# (day) | 3.5 (1‑7) | 7.0 (3‑7)
AUC (day*μg/mL) | 596 ± 245 | 653.0 ± 132
t1/2 (day) | 9.8 ± 3.1 | 11.0 ± 2.5
Bioavailability (%) | Not determined | 73.2 ± 14.8

#Median and range

In a cross‑study comparison of the pharmacokinetics in healthy laboratory cats and cats with naturally occurring osteoarthritis, the median time to maximum concentration (Tmax) was approximately 3.5 days longer in cats with osteoarthritis compared to healthy cats. Cmax was greater in healthy cats compared to cats with osteoarthritis. Overall drug exposure (AUC) and half‑life were similar between healthy cats and cats with osteoarthritis. Compared to an intravenous dose, subcutaneously-administered frunevetmab had a bioavailability of approximately 73% in cats with osteoarthritis.
In a field effectiveness study at the label dose in cats with osteoarthritis, steady‑state was achieved after approximately 2 doses.

EFFECTIVENESS

Because of the limitations currently inherent in studies designed to assess chronic pain and the response to drugs intended to control chronic pain in cats, a weight of evidence approach was employed to determine if the overall evidence supported the conclusion that SOLENSIA was effective for the control of pain associated with osteoarthritis in cats. Based on current thinking, the endpoints used to evaluate the effectiveness of SOLENSIA for the control of osteoarthritic pain in cats are observer-reported measures conducted by either owners or veterinarians. When taken together, the results of the two studies described below demonstrate the effectiveness of SOLENSIA for the control of pain associated with osteoarthritis in cats. Additional information related to the evaluation of these studies, including the study endpoints, is available in the Freedom of Information Summary available at https://animaldrugsatfda.fda.gov.
Field Effectiveness Study #1
A 56‑day, masked, randomized, controlled field study was conducted at 14 U.S. veterinary clinics. The study enrolled 126 client‑owned cats with clinical signs of osteoarthritis (OA) confirmed by radiography and orthopedic examination; enrolled cats weighed 3.3 to 10.5 kg and were over 6 months old. The enrolled cats were randomized to treatment with frunevetmab injection (n=85) manufactured similar to SOLENSIA or vehicle control (n=41), administered subcutaneously on Days 0 and 28 or intravenously on Day 0 and subcutaneously on Day 28. Cats were dosed with frunevetmab injection or vehicle control based on body weight (2.5‑7 kg cats received 1 mL, 7.1‑14 kg cats received 2 mL).
Outcome measures for the control of pain associated with OA included comparison of the owner’s evaluation of Client Specific Outcomes Measures (CSOM) at Days 14, 28, 42, and 56 compared to baseline (Day 0, before treatment); Owner Global Assessments on Days 28 and 56; and total orthopedic pain score completed by the veterinarian at screening and on Days 28 and 56. For the CSOM, treatment success was defined as a reduction of at least 2 in the total CSOM score compared with the score at baseline. Cats that had an increase in any individual CSOM activity score (regardless of the total CSOM score) were considered treatment failures. For the Owner Global Assessment, success was defined as an owner’s impression of the response to treatment as Good or Excellent (versus Fair or Poor). Success was not defined for the veterinarian-assessed total orthopedic pain score. The proportion of cats considered treatment successes based on the owner CSOM assessment and the Owner Global Assessment was greater in the frunevetmab injection group compared to the control group for all assessments. The mean total orthopedic pain score was lower in the frunevetmab injection group compared to the control group at all post‑dosing assessments.
Table 4. Percent CSOM Success by Assessment Day

Study Day | Frunevetmab Injection (%) | Vehicle Control (%)
14 | 61.8 | 60.6
28 | 68.6 | 55.9
42 | 73.5 | 55.9
56 | 80.0 | 47.1

Table 5. Percent Owner Global Assessment Success by Assessment Day

Study Day | Frunevetmab Injection (%) | Vehicle Control (%)
28 | 63.2 | 26.3
56 | 71.1 | 32.4

Table 6. Mean Veterinarian-Assessed Total Orthopedic Pain Score by Assessment Day

Study Day | Frunevetmab Injection (change from baseline) | Vehicle Control (change from baseline)
Screening | 31.88 | 32.25
28 | 27.08 (-4.8) | 28.03 (-4.22)
56 | 25.69 (-6.19) | 27.75 (-4.5)

Field Effectiveness Study #2
A 112-day, masked, randomized, controlled field study was conducted at 21 U.S. veterinary clinics. The study enrolled 275 client-owned cats with clinical signs of osteoarthritis (OA) confirmed by radiography and orthopedic examination; enrolled cats weighed 2.5 to 11.4 kg and were 1.6 to 22.4 years old. The enrolled cats were randomized to treatment with SOLENSIA (n=182) or vehicle control (n=93), administered subcutaneously on Days 0, 28, and 56. Cats were dosed with SOLENSIA (frunevetmab injection) or vehicle control based on body weight (2.5-7 kg cats received 1 mL, 7.1-14 kg cats received 2 mL).
The primary outcome measure for success for the control of pain associated with OA was comparison of the owner’s evaluation of CSOM at Day 56 compared to baseline (Day 0, before treatment). Treatment success was defined as a reduction of at least 2 in the total CSOM score at Day 56 compared with the score at baseline. Cats that had an increase in any individual CSOM activity score (regardless of the total CSOM score) or that received rescue analgesia prior to Day 56 were considered treatment failures. Secondary outcome measures included the total CSOM score on Days 28 and 84; Owner Global Assessments on Days 28, 56, and 84; and total orthopedic pain score completed by the veterinarian on Days 28, 56, and 84. For the Owner Global Assessment, success was defined as an owner’s impression of the response to treatment as Good or Excellent (versus Fair or Poor). Success was not defined for the veterinary-assessed total orthopedic pain score. The proportion of cats considered treatment successes based on the owner CSOM assessment and the Owner Global Assessment was greater in the SOLENSIA group compared to the control group for all assessments. The mean total orthopedic pain score was lower in the SOLENSIA group compared to the control group at all post‑dosing assessments.
Table 7. Percent CSOM Success by Assessment Day

Study Day | Solensia (%) | Vehicle Control (%)
28 | 66.9 | 51.6
56 | 75.1 | 64.8
84 | 76.5 | 67.3

Table 8. Percent Owner Global Assessment Success by Assessment Day

Study Day | Solensia (%) | Vehicle Control (%)
28 | 39.3 | 30.4
56 | 59.3 | 48.3
84 | 64.6 | 57.8

Table 9. Mean Veterinarian-Assessed Total Orthopedic Pain Score by Assessment Day

Study Day | Solensia (change from baseline) | Vehicle Control (change from baseline)
Screening | 34.11 | 33.6
28 | 28.68 (-5.43) | 29.1 (-4.5)
56 | 27.52 (-6.59) | 28.67 (-4.93)
84 | 27.29 (-6.82) | 28.54 (-5.06)

TARGET ANIMAL SAFETY

Frunevetmab injection was administered subcutaneously to healthy seven to eight‑month-old cats (8 cats per group) at doses of 2.8 mg/kg (1X), 8.4 mg/kg (3X), and 14 mg/kg (5X) every 28 days for six consecutive doses. The control group (8 cats) received vehicle control injections. No clinically significant changes related to frunevetmab were observed among the cats for physical examination, lameness evaluation, and body weight.

The most common findings included vomiting and diarrhea observed sporadically in all groups. The highest frequency of vomiting occurred in the 1X group. Clinically relevant skin findings included abrasions, alopecia, or scabs mostly around the face and ears. These findings were noted in three 1X cats, three 3X cats, and one 5X cat. Another 1X cat developed a 2 cm ventral neck lesion following clipping and blood collection on Day 87. Although the initial irritation appeared related to the clipping, the unexpectedly severe and persistent pruritus and prolonged recovery were deemed possibly drug-related. The ulcerated skin lesion healed when self‑trauma was prevented including the placement of an e‑collar for the remainder of the study.

Flinching was occasionally associated with injections, most frequently noted during the first dosing in all dosing groups. Occasionally, scabs, small abrasions, or spot of alopecia were observed at the injection sites in all dosing groups. A few cats had transient swelling at injection sites.

Body tremors and shivering were noted in one 3X cat on Day 28.

Serum creatinine values in females were significantly higher in the 5X group compared to controls (P < 0.10). Creatinine values on Day 28 were significantly higher (P= 0.0239) in the 1X group compared to the control group. On Day 112, values were significantly higher (P = 0.0443) in the 5X group compared to the control group. Creatinine values did not exceed the reference ranges in cats of either sex at any time point.

There was one 1X cat with mild focal discoloration of the left tibiofemoral joint cruciate ligament on gross pathology. There was no correlative pathology on microscopic examination.

No lameness was reported in this cat or any cat over the course of this study.

One 1X cat had a small amount of bilirubinuria on Day 43. This cat had dark urine and hematuria on Days 43‑45 with no evidence of UTI on urinalysis. The cat responded to a canned prescription urinary diet and recovered. This cat also vomited food, bile or hair on three days and had diarrhea or dark, tarry stools on two days. Another 3X cat had a small amount of bilirubinuria on Day 83 and orange colored urine. This cat also had elevated serum lactate dehydrogenase activity at three time points.

There was one 5X cat that had a small amount of bilirubinuria at the end of the study with lipid sediment. This cat also had focal hepatic lipidosis on histopathology.

STORAGE CONDITIONS

SOLENSIA should be stored upright in a refrigerator, between 35°– 46°F (2°– 8°C). Do not freeze. Protect from light. See in-use instructions provided in the DOSAGE AND ADMINISTRATION section.

HOW SUPPLIED

SOLENSIA is supplied as a sterile buffered solution of 7 mg/mL of frunevetmab in single‑use 4 mL glass vials containing an extractable volume of 1 mL of clear solution with a butyl rubber stopper and aluminum overseal. Vials are available in cartons containing 2 or 6 vials.

Approved by FDA under NADA # 141-546

zoetis

Distributed by:
Zoetis Inc.
Kalamazoo, MI 49007

August 2021

68000005

PRINCIPAL DISPLAY PANEL - 6-ct Carton Label

66000073